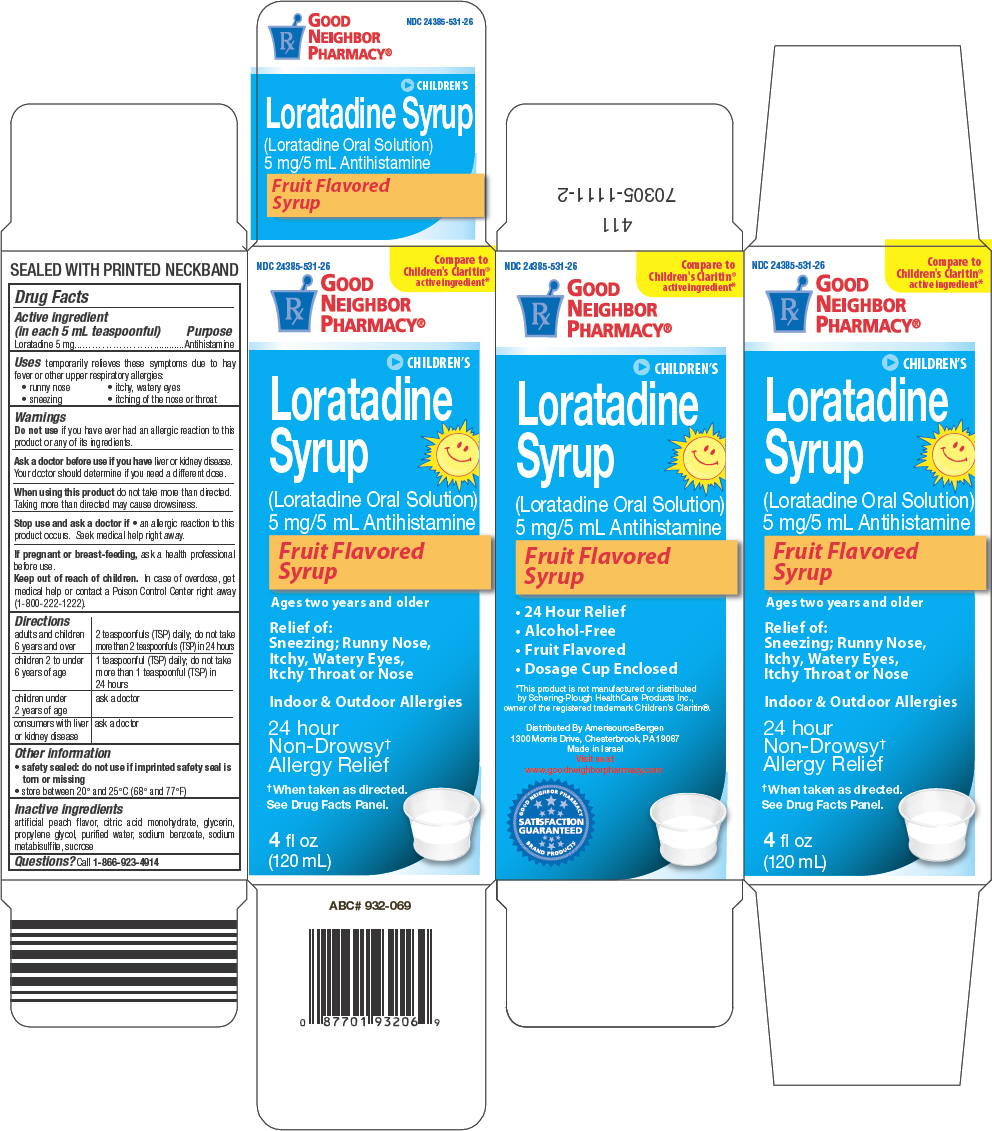 DRUG LABEL: Good Neighbor Pharmacy 
NDC: 24385-531 | Form: SOLUTION
Manufacturer: AmerisourceBergen
Category: otc | Type: HUMAN OTC DRUG LABEL
Date: 20200624

ACTIVE INGREDIENTS: Loratadine 5 mg/5 mL
INACTIVE INGREDIENTS: citric acid monohydrate; glycerin; propylene glycol; water; sodium benzoate; sodium metabisulfite; sucrose

Good Neighbor Pharmacy® Children's Loratadine

Drug Facts

Active ingredient (in each 5 mL teaspoonful)

Loratadine 5 mg

Purpose

Antihistamine

Uses

temporarily relieves these symptoms due to hay fever or other upper respiratory allergies:

- runny nose
- itchy, watery eyes
- sneezing
- itching of the nose or throat

Warnings

Do not use if you have ever had an allergic reaction to this product or any of its ingredients.

Ask a doctor before use if you have liver or kidney disease. Your doctor should determine if you need a different dose.

When using this product do not take more than directed. Taking more than directed may cause drowsiness.

Stop use and ask a doctor if

- an allergic reaction to this product occurs. Seek medical help right away.

PREGNANCY OR BREAST FEEDING

If pregnant or breast-feeding, ask a health professional before use.

Keep out of reach of children. In case of overdose, get medical help or contact a Poison Control Center right away (1-800-222-1222).

Directions

adults and children 6 years and over | 2 teaspoonfuls (TSP) daily; do not take more than 2 teaspoonfuls (TSP) in 24 hours
children 2 to under 6 years of age | 1 teaspoonful (TSP) daily; do not take more than 1 teaspoonful (TSP) in 24 hours
children under 2 years of age | ask a doctor
consumers with liver or kidney disease | ask a doctor

Other information

- safety sealed: do not use if imprinted safety seal is torn or missing
- store between 20° and 25°C (68° and 77°F)

Inactive ingredients

artificial peach flavor, citric acid monohydrate, glycerin, propylene glycol, purified water, sodium benzoate, sodium metabisulfite, sucrose

Questions?

Call 1-866-923-4914

Distributed By AmerisourceBergen
1300 Morris Drive, Chesterbrook, PA 19087

PRINCIPAL DISPLAY PANEL - 120 mL Bottle Carton

NDC 24385-531-26

Compare to
Children's Claritin®
active ingredient*

GOOD
NEIGHBOR
PHARMACY®

CHILDREN'S

Loratadine
Syrup

(Loratadine Oral Solution)
5 mg/5 mL Antihistamine

Fruit Flavored
Syrup

Ages two years and older

Relief of:
Sneezing; Runny Nose,
Itchy, Watery Eyes,
Itchy Throat or Nose

Indoor & Outdoor Allergies

24 hour
Non-Drowsy†
Allergy Relief

† When taken as directed.
See Drug Facts Panel.

4 fl oz
(120 mL)